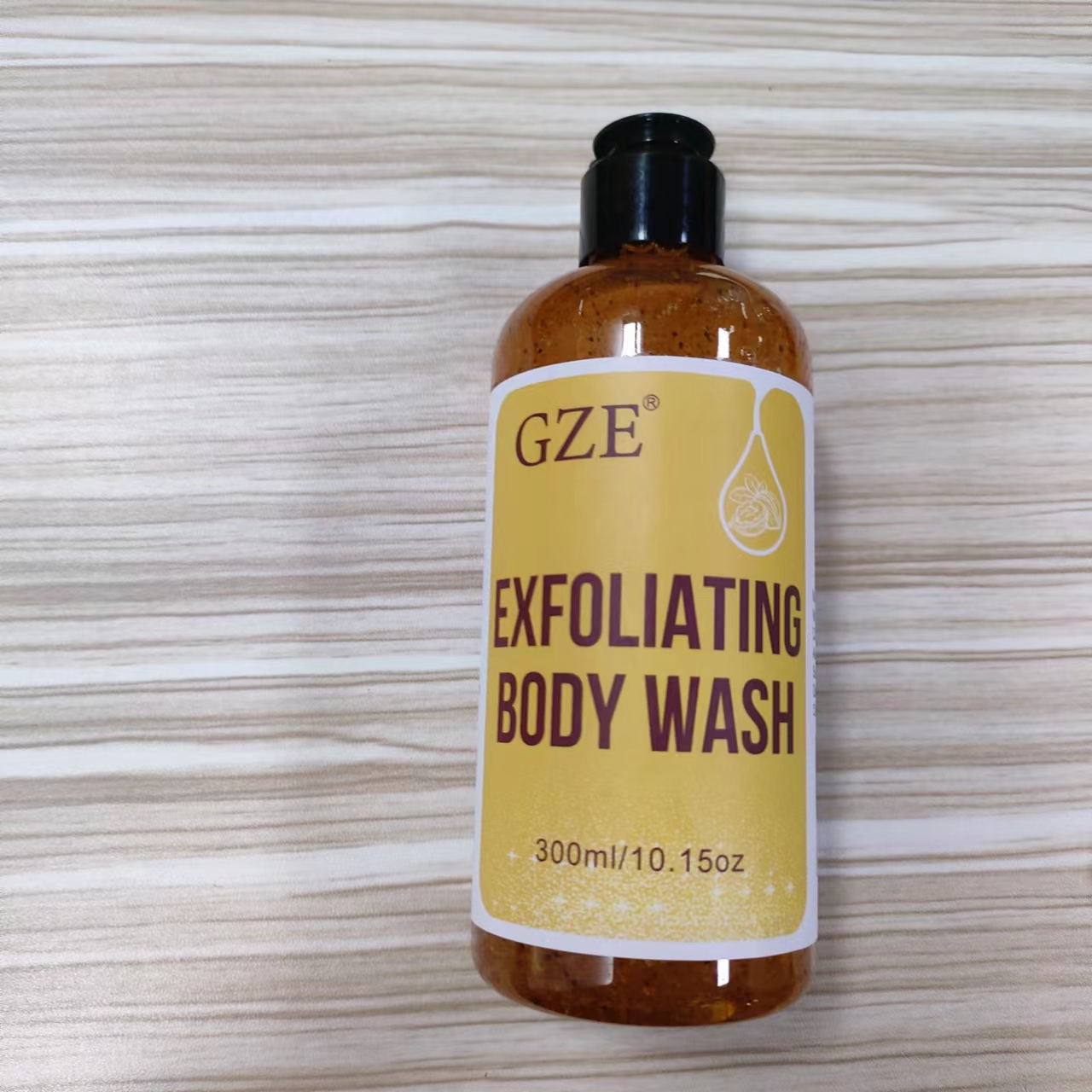 DRUG LABEL: GZE EXFOLIATING BODY WASH
NDC: 74458-239 | Form: LOTION
Manufacturer: Guangzhou Yilong Cosmetics Co., Ltd
Category: otc | Type: HUMAN OTC DRUG LABEL
Date: 20241115

ACTIVE INGREDIENTS: COCONUT SHELL 5 g/100 mL; JUGLANS REGIA SHELL 8 g/100 mL
INACTIVE INGREDIENTS: CITRIC ACID; SODIUM HYDROXIDE; GLYCERIN; AQUA; POWDERED CELLULOSE

GZE EXFOLIATING BODY WASH

ACTIVE INGREDIENT

Juglans Regia (Walnut) Shell Powder

8

Cocos Nucifera (Coconut) Shell Powder

5

INACTIVE INGREDIENT

Aqua

Glycerin

Cellulose

Citric Acid

Sodium Hydroxide

Fragrance

INDICATIONS AND USAGE

Apply an appropriate amount of exfoliating body wash to your body and rub it with a bath ball for about 5 minutes, rubbing the exfoliated areas a few more times, and finally rinse off with water.

PURPOSE

Exfoliating.

WARNINGS

For external use only.

Stop use and ask a doctor if rash occurs.

Do not use on damaged or broken skin.

When using this product keep out of eyes. Rinse with water to remove.

Keep out of reach of children. If swallowed, get medical help or contact a Poison Control Center right away.

DOSAGE AND ADMINISTRATION

Apply an appropriate amount of exfoliating body wash to your body and rub it with a bath ball for about 5 minutes, rubbing the exfoliated areas a few more times, and finally rinse off with water.